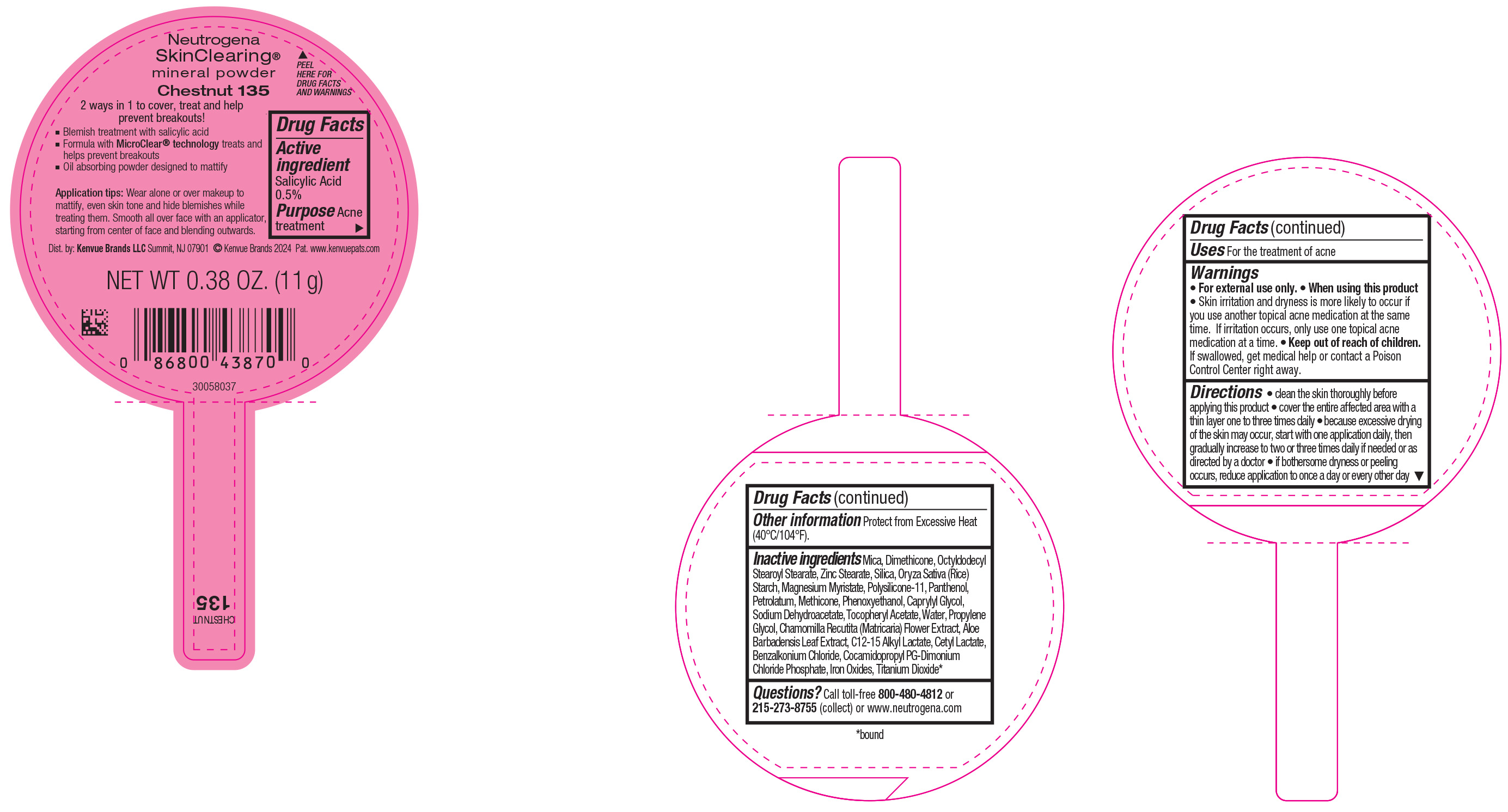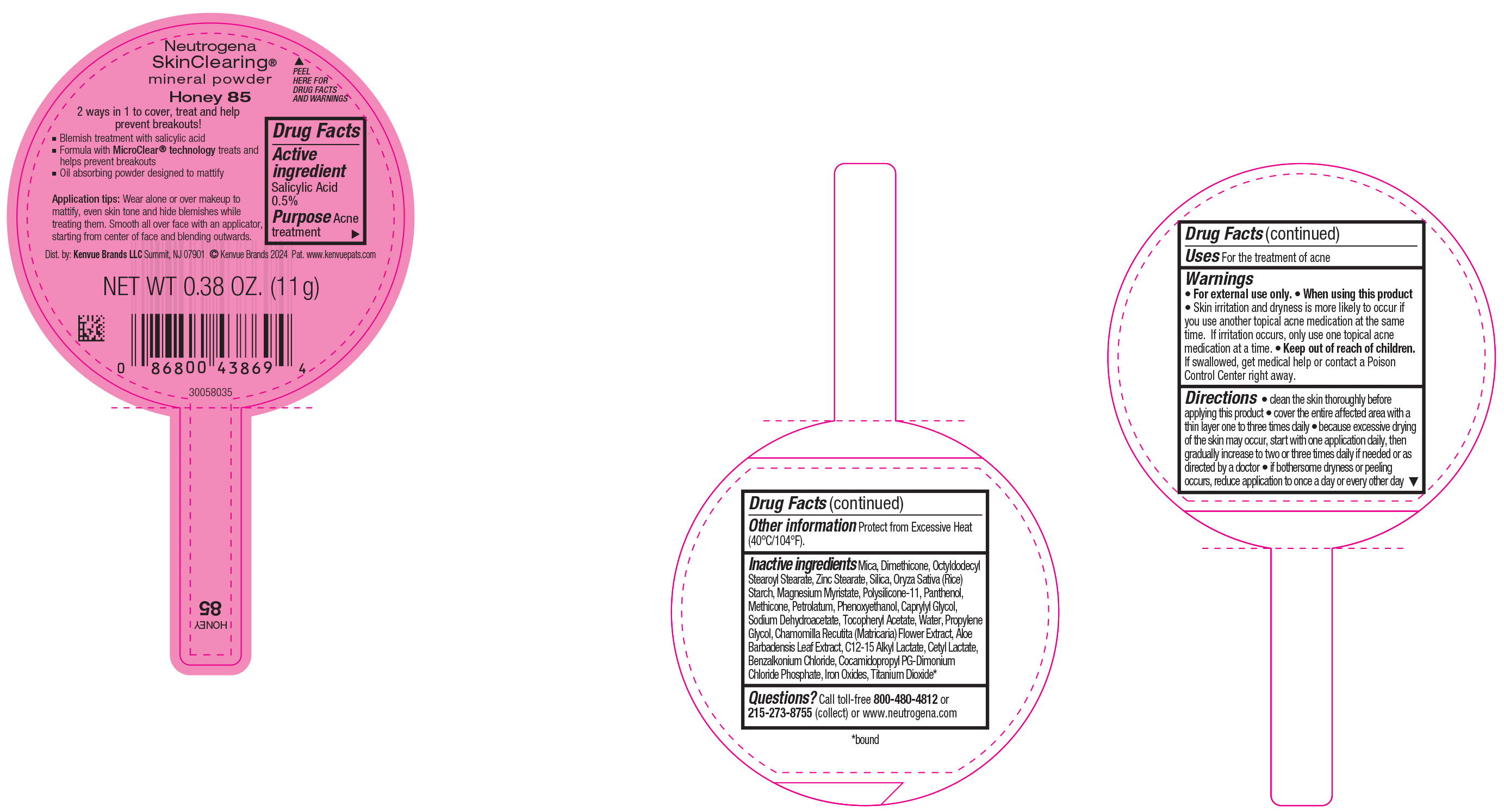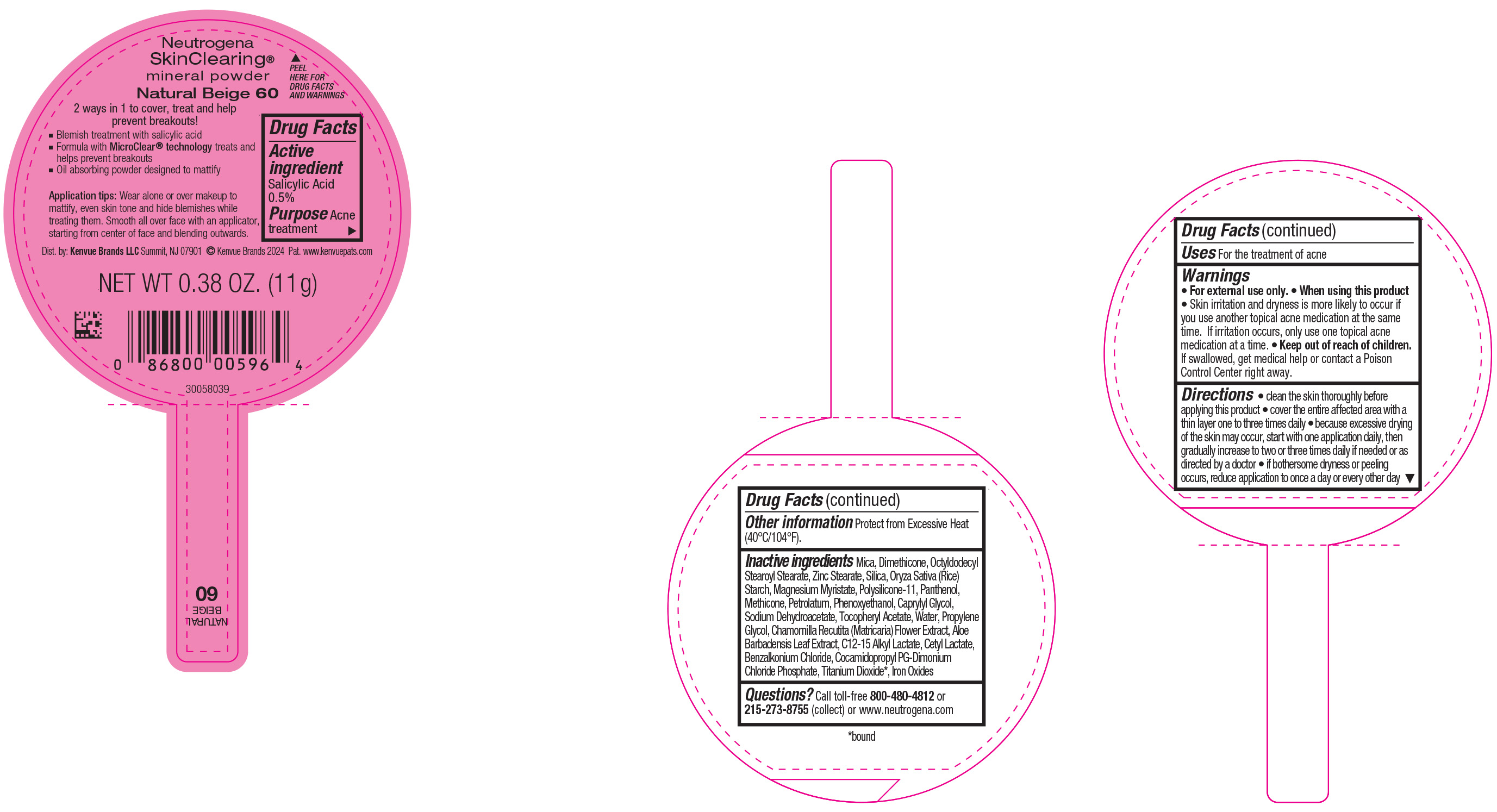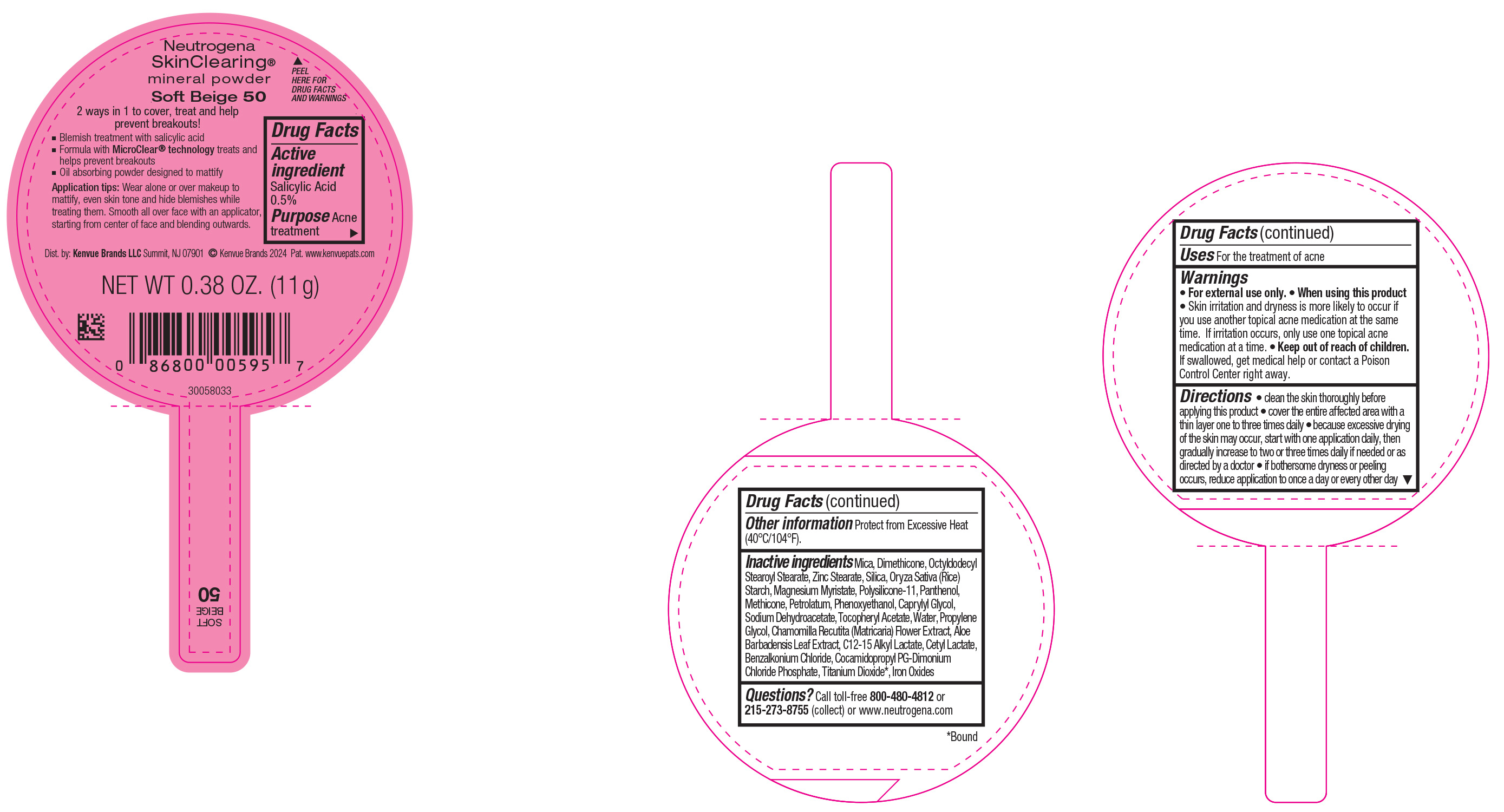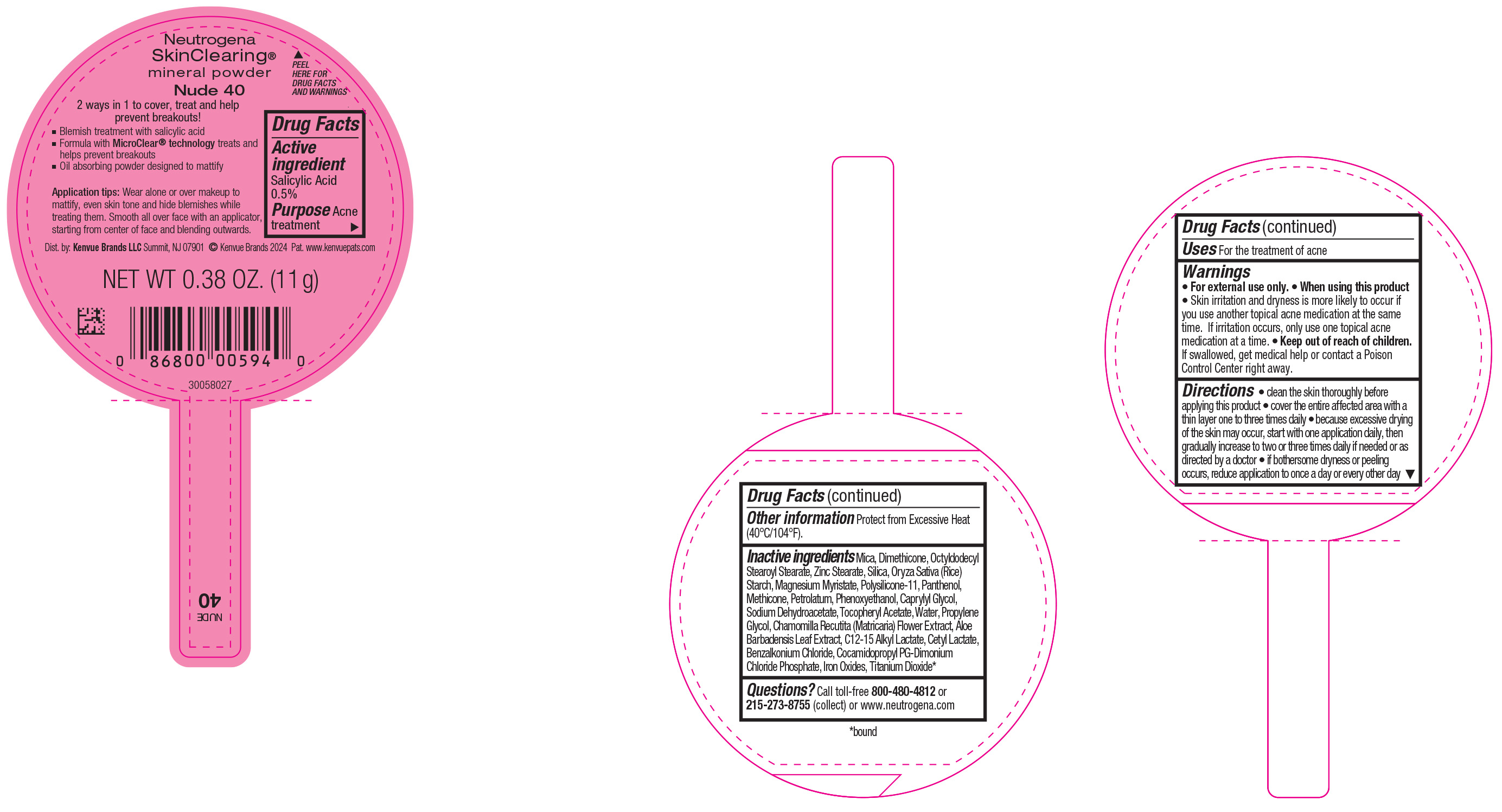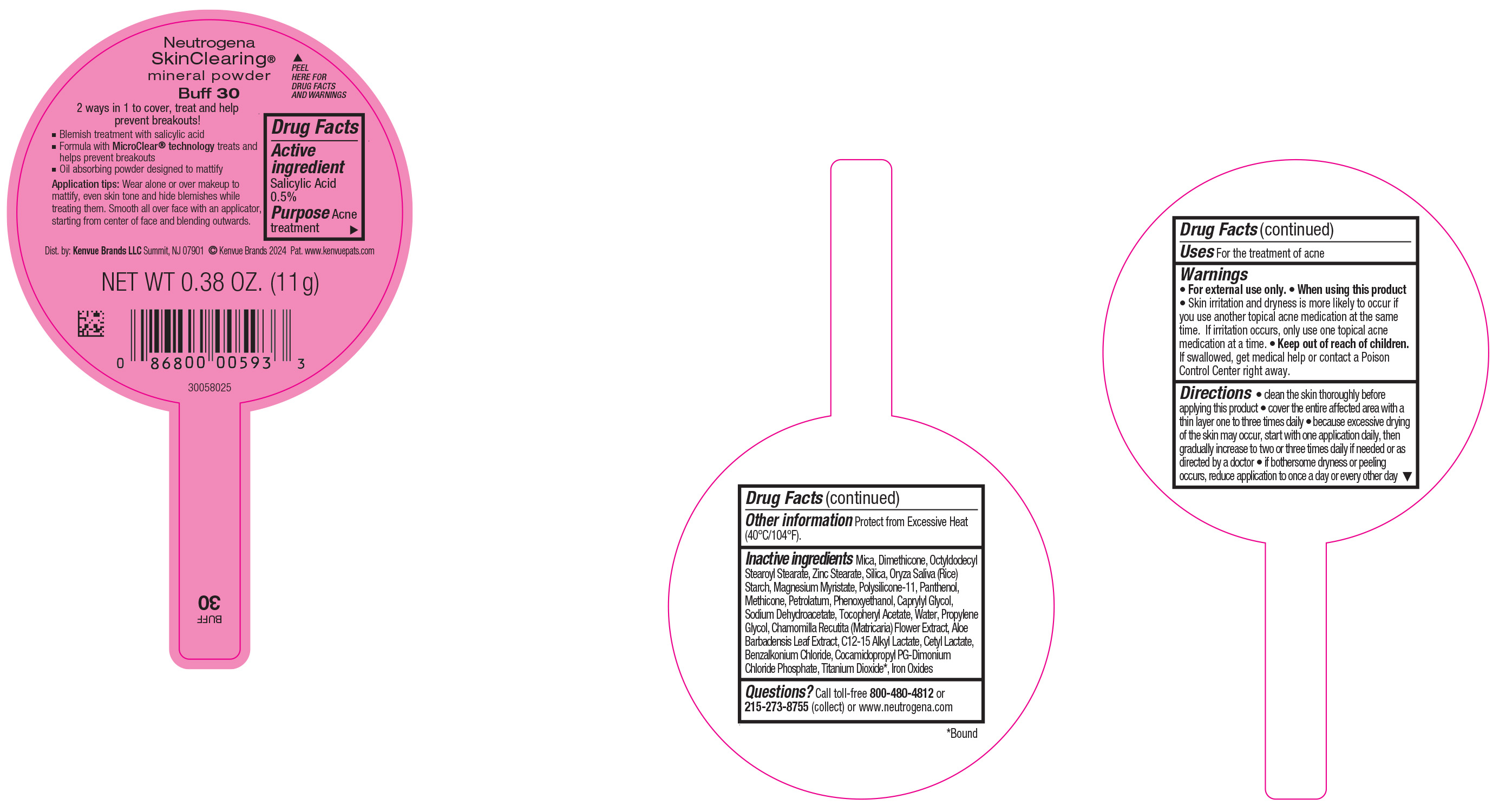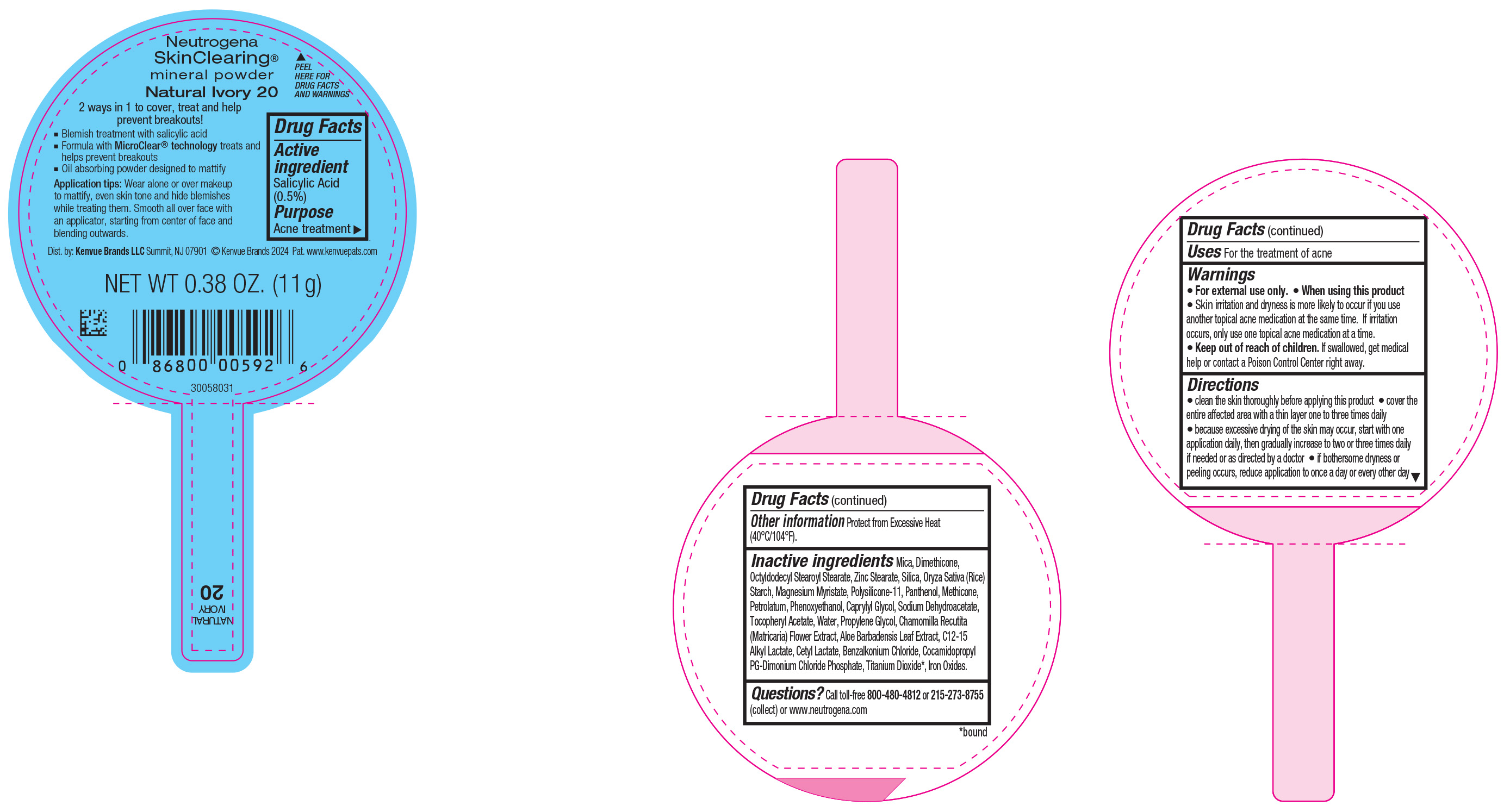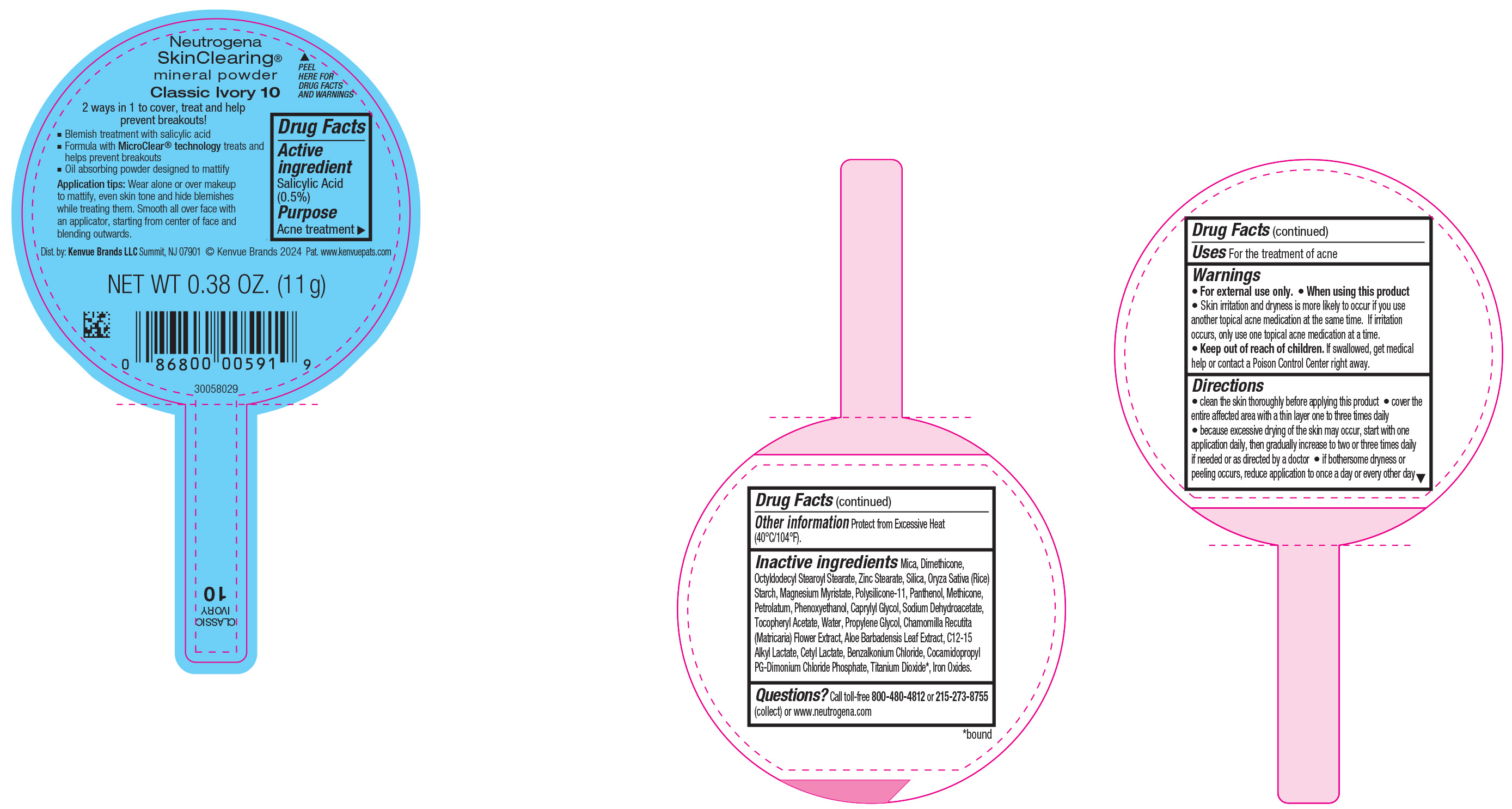 DRUG LABEL: Neutrogena SkinClearing Mineral Powder Honey 85
NDC: 69968-0834 | Form: POWDER
Manufacturer: Kenvue Brands LLC
Category: otc | Type: HUMAN OTC DRUG LABEL
Date: 20241113

ACTIVE INGREDIENTS: SALICYLIC ACID 5 mg/1 g
INACTIVE INGREDIENTS: DIMETHICONE; MICA; DIMETHICONE/VINYL DIMETHICONE CROSSPOLYMER (SOFT PARTICLE); PHENOXYETHANOL; ALPHA-TOCOPHEROL ACETATE; PROPYLENE GLYCOL; CHAMOMILE; WATER; ALOE VERA LEAF; C12-15 ALKYL LACTATE; BENZALKONIUM CHLORIDE; TITANIUM DIOXIDE; SILICON DIOXIDE; METHICONE (20 CST); PETROLATUM; COCAMIDOPROPYL PG-DIMONIUM CHLORIDE PHOSPHATE; STARCH, RICE; MAGNESIUM MYRISTATE; PANTHENOL; CAPRYLYL GLYCOL; SODIUM DEHYDROACETATE; CETYL LACTATE; FERRIC OXIDE RED; OCTYLDODECYL STEAROYL STEARATE; ZINC STEARATE

Neutrogena SkinClearing Mineral Powder Chestnut 135
Neutrogena SkinClearing Mineral Powder Honey 85
Neutrogena SkinClearing Mineral Powder Natural Beige 60
Neutrogena SkinClearing Mineral Powder Soft Beige 50
Neutrogena SkinClearing Mineral Powder Nude 40
Neutrogena SkinClearing Mineral Powder Buff 30
Neutrogena SkinClearing Mineral Powder Natural Ivory 20
Neutrogena SkinClearing Mineral Powder Classic Ivory 10

Drug Facts

Active ingredient

Salicylic Acid (0.5%)

Purpose

Acne treatment

Use

For the treatment of acne

Warnings

For external use only.

When using this product

Skin irritation and dryness is more likely to occur if you use another topical acne medication at the same time. If irritation occurs, only use one topical acne medication at a time.

Keep out of reach of children. If swallowed, get medical help or contact a Poison Control Center right away.

Directions

• clean the skin thoroughly before applying this product

• cover the entire affected area with a thin layer one to three times daily

• because excessive drying of the skin may occur, start with one application daily, then gradually increase to two or three times daily if needed or as directed by a doctor

• if bothersome dryness or peeling occurs, reduce application to once a day or every other day

Other Information

Protect from Excessive Heat (40°C/104°F).

Inactive ingredients

Mica, Dimethicone, Octyldodecyl Stearoyl Stearate, Zinc Stearate, Silica, Oryza Sativa (Rice) Starch, Magnesium Myristate, Polysilicone-11, Panthenol, Petrolatum, Methicone, Phenoxyethanol, Caprylyl Glycol, Sodium Dehydroacetate, Tocopheryl Acetate, Water, Propylene Glycol, Chamomilla Recutita (Matricaria) Flower Extract, Aloe Barbadensis Leaf Extract, C12-15 Alkyl Lactate, Cetyl Lactate, Benzalkonium Chloride, Cocamidopropyl PG-Dimonium Chloride Phosphate, Iron Oxides, Titanium Dioxide*.

Questions?

Call toll-free 800-480-4812 or 215-273-8755 (collect) or www.neutrogena.com

Distributed by: Kenvue Brands LLC Summit, NJ 07901

PRINCIPAL DISPLAY PANEL - 11 g Container Label - Chestnut 135

Neutrogena

SkinClearing®

mineral powder

Chestnut 135

2 ways in 1 to cover, treat and help

prevent breakouts!

▪ Blemish treatment with salicylic acid

▪ Formula with MicroClear® technology treats and

helps prevent breakouts

▪ Oil absorbing powder designed to mattify

Application tips: Wear alone or over makeup to

mattify, even skin tone and hide blemishes while

treating them. Smooth all over face with an applicator,

starting from center of face and blending outwards.

NET WT 0.38 OZ. (11 g)

PRINCIPAL DISPLAY PANEL - 11 g Container Label - Natural Beige 60

Neutrogena

SkinClearing®

mineral powder

Natural Beige 60

2 ways in 1 to cover, treat and help

prevent breakouts!

▪ Blemish treatment with salicylic acid

▪ Formula with MicroClear® technology treats and

helps prevent breakouts

▪ Oil absorbing powder designed to mattify

Application tips: Wear alone or over makeup to

mattify, even skin tone and hide blemishes while

treating them. Smooth all over face with an applicator,

starting from center of face and blending outwards.

NET WT 0.38 OZ. (11 g)

PRINCIPAL DISPLAY PANEL - 11 g Container Label - Honey 85

Neutrogena

SkinClearing®

mineral powder

Honey 85

2 ways in 1 to cover, treat and help

prevent breakouts!

▪ Blemish treatment with salicylic acid

▪ Formula with MicroClear® technology treats and

helps prevent breakouts

▪ Oil absorbing powder designed to mattify

Application tips: Wear alone or over makeup to

mattify, even skin tone and hide blemishes while

treating them. Smooth all over face with an applicator,

starting from center of face and blending outwards.

NET WT 0.38 OZ. (11 g)

PRINCIPAL DISPLAY PANEL - 11 g Container Label - Soft Beige 50

Neutrogena

SkinClearing®

mineral powder

Soft Beige 50

2 ways in 1 to cover, treat and help

prevent breakouts!

▪ Blemish treatment with salicylic acid

▪ Formula with MicroClear® technology treats and

helps prevent breakouts

▪ Oil absorbing powder designed to mattify

Application tips: Wear alone or over makeup to

mattify, even skin tone and hide blemishes while

treating them. Smooth all over face with an applicator,

starting from center of face and blending outwards.

NET WT 0.38 OZ. (11 g)

PRINCIPAL DISPLAY PANEL - 11 g Container Label - Nude 40

Neutrogena

SkinClearing®

mineral powder

Nude 40

2 ways in 1 to cover, treat and help

prevent breakouts!

▪ Blemish treatment with salicylic acid

▪ Formula with MicroClear® technology treats and

helps prevent breakouts

▪ Oil absorbing powder designed to mattify

Application tips: Wear alone or over makeup to

mattify, even skin tone and hide blemishes while

treating them. Smooth all over face with an applicator,

starting from center of face and blending outwards.

NET WT 0.38 OZ. (11 g)

PRINCIPAL DISPLAY PANEL - 11 g Container Label - Buff 30

Neutrogena

SkinClearing®

mineral powder

Buff 30

2 ways in 1 to cover, treat and help

prevent breakouts!

▪ Blemish treatment with salicylic acid

▪ Formula with MicroClear® technology treats and

helps prevent breakouts

▪ Oil absorbing powder designed to mattify

Application tips: Wear alone or over makeup to

mattify, even skin tone and hide blemishes while

treating them. Smooth all over face with an applicator,

starting from center of face and blending outwards.

NET WT 0.38 OZ. (11 g)

PRINCIPAL DISPLAY PANEL - 11 g Container Label - Natural Ivory 20

Neutrogena

SkinClearing®

mineral powder

Natural Ivory 20

2 ways in 1 to cover, treat and help

prevent breakouts!

▪ Blemish treatment with salicylic acid

▪ Formula with MicroClear® technology treats and

helps prevent breakouts

▪ Oil absorbing powder designed to mattify

Application tips: Wear alone or over makeup to

mattify, even skin tone and hide blemishes while

treating them. Smooth all over face with an applicator,

starting from center of face and blending outwards.

NET WT 0.38 OZ. (11 g)

PRINCIPAL DISPLAY PANEL - 11 g Container Label - Classic Ivory 10

Neutrogena

SkinClearing®

mineral powder

Classic Ivory 10

2 ways in 1 to cover, treat and help

prevent breakouts!

▪ Blemish treatment with salicylic acid

▪ Formula with MicroClear® technology treats and

helps prevent breakouts

▪ Oil absorbing powder designed to mattify

Application tips: Wear alone or over makeup to

mattify, even skin tone and hide blemishes while

treating them. Smooth all over face with an applicator,

starting from center of face and blending outwards.

NET WT 0.38 OZ. (11 g)